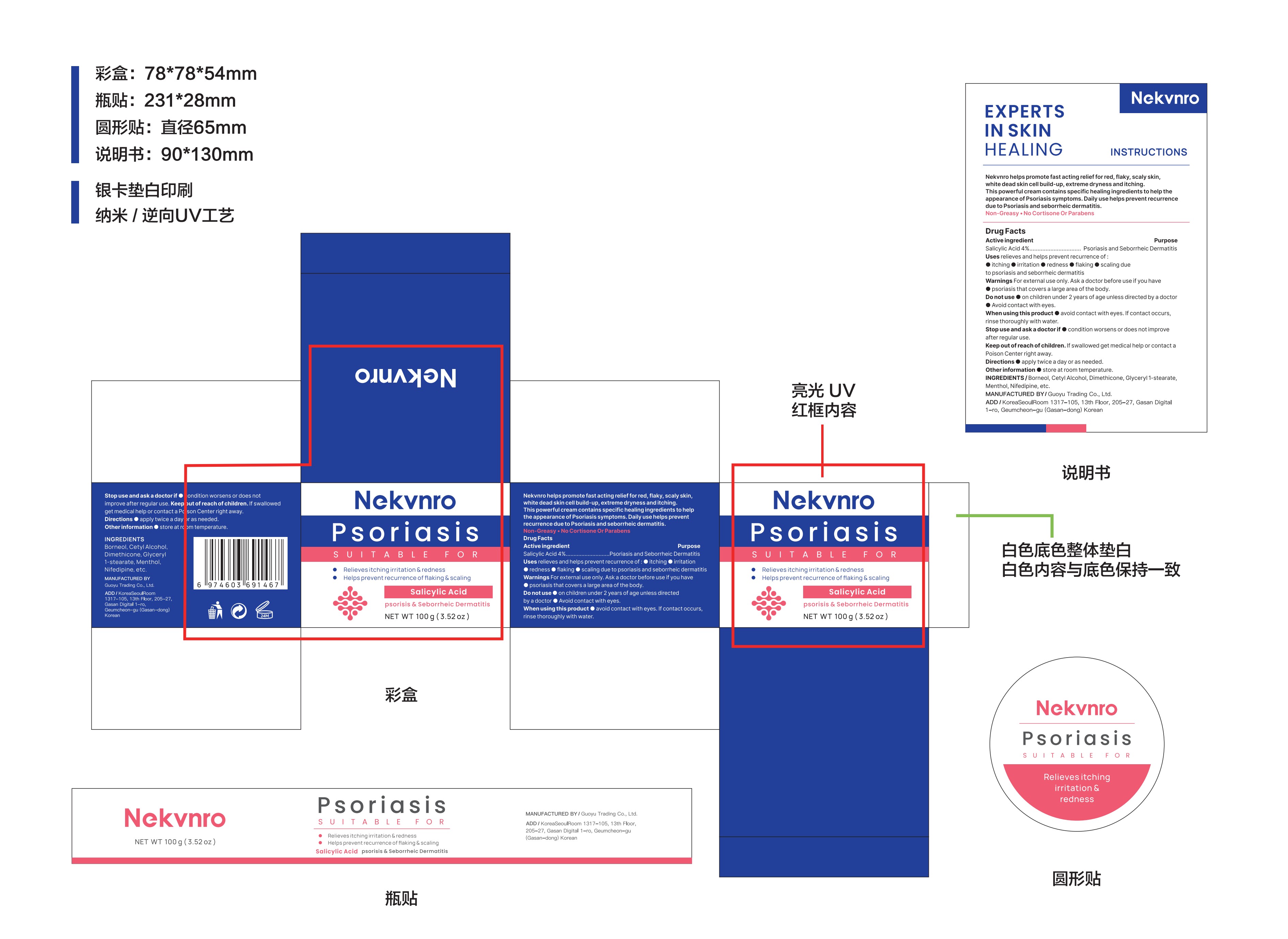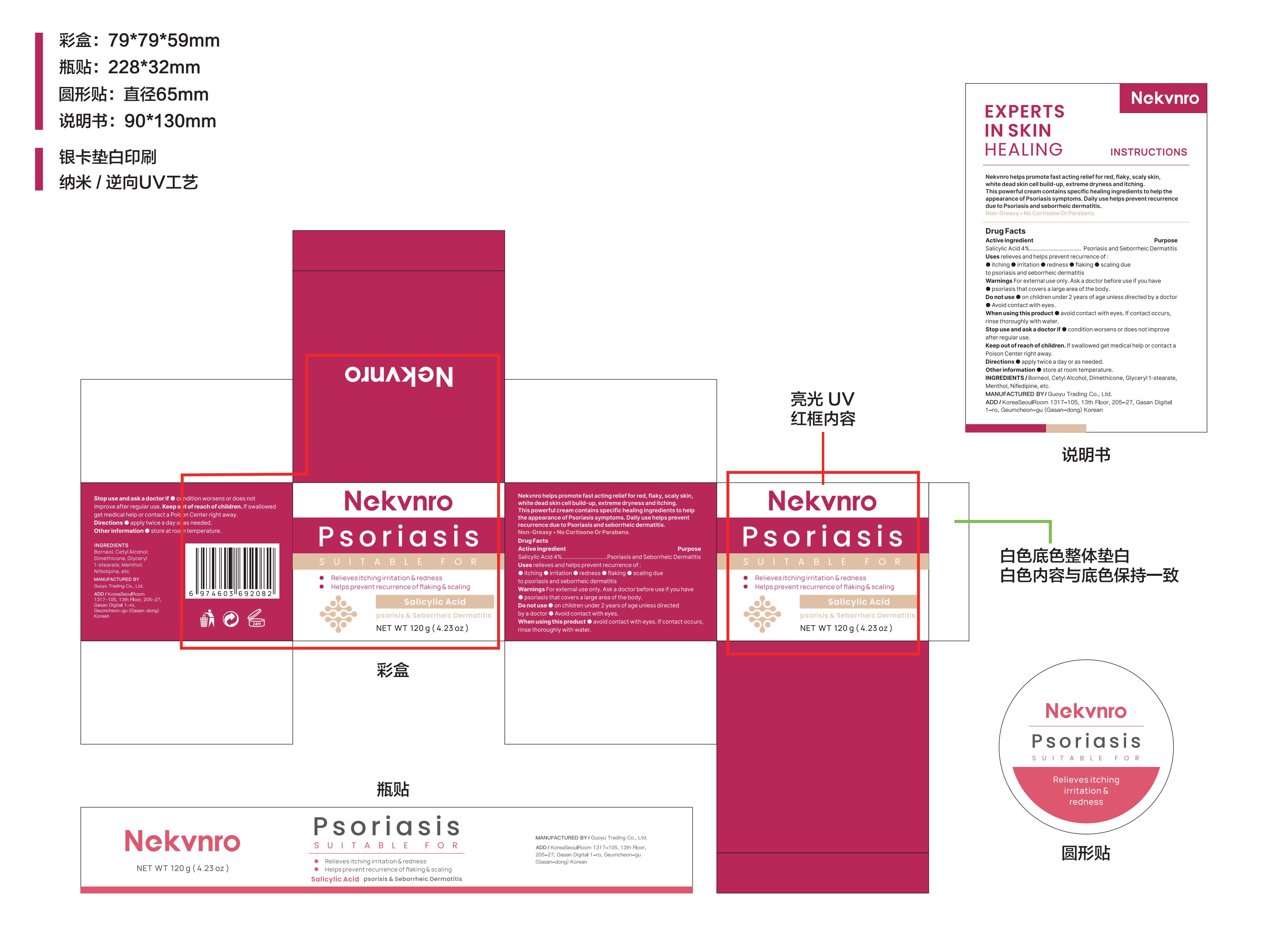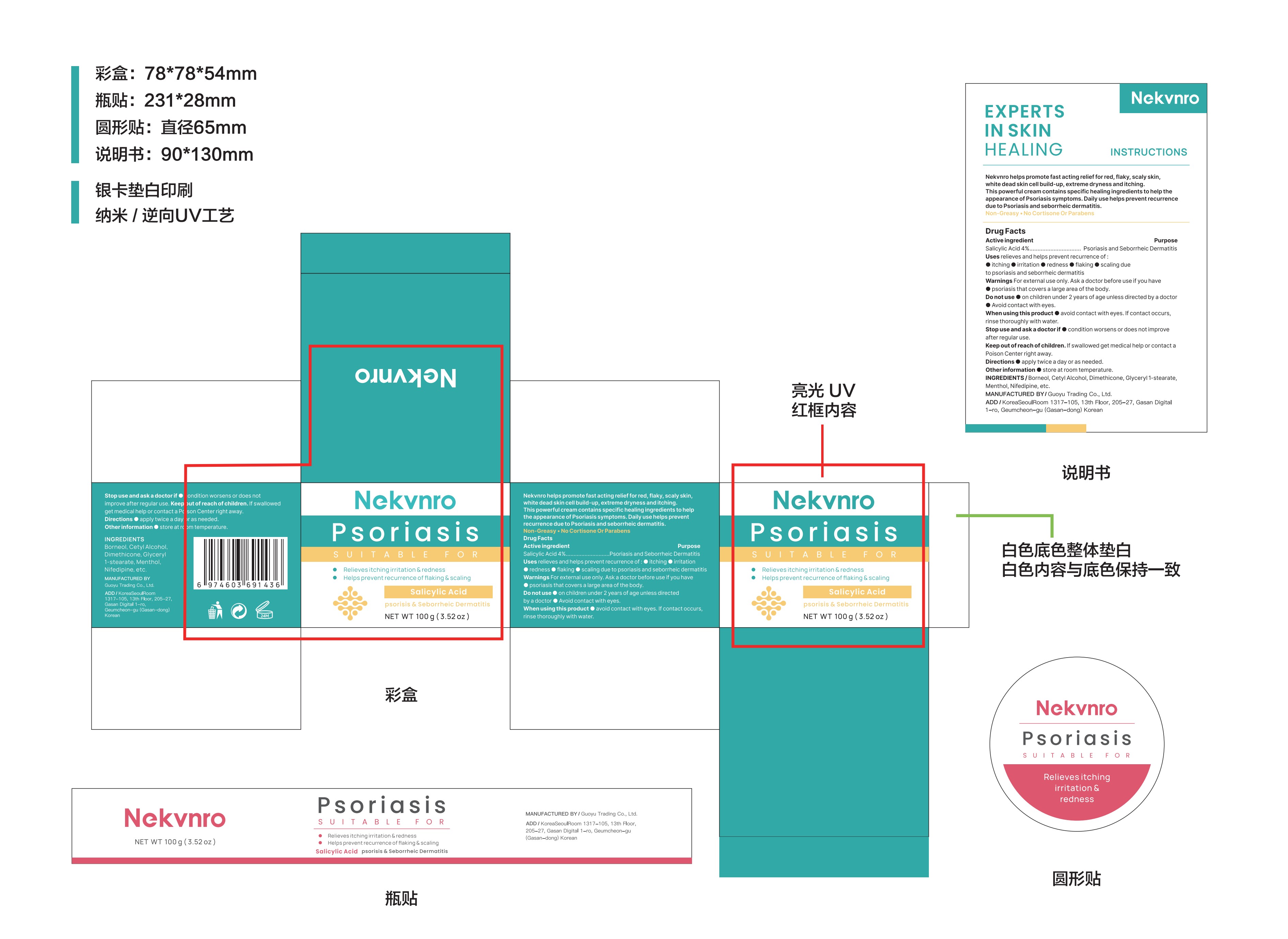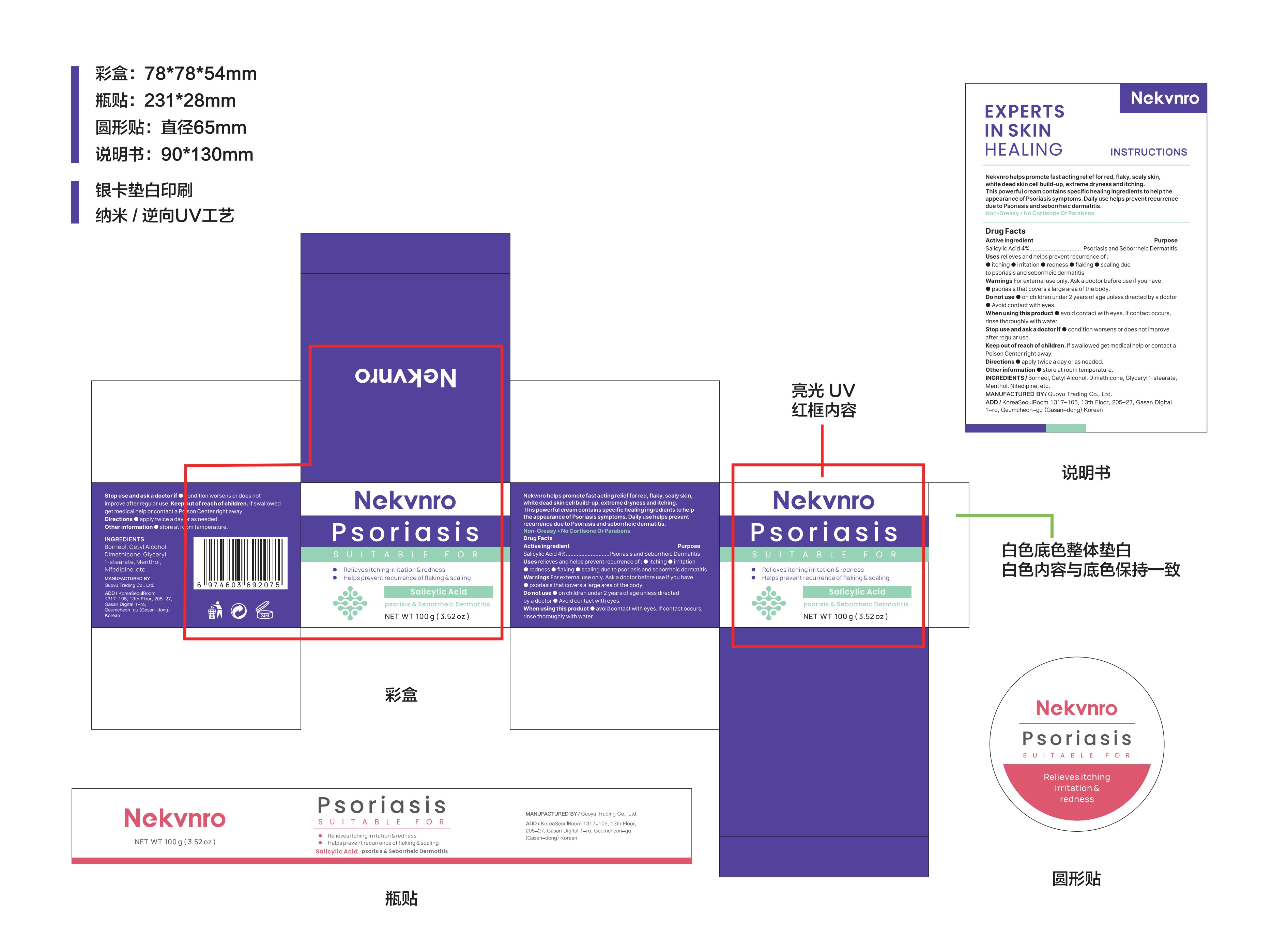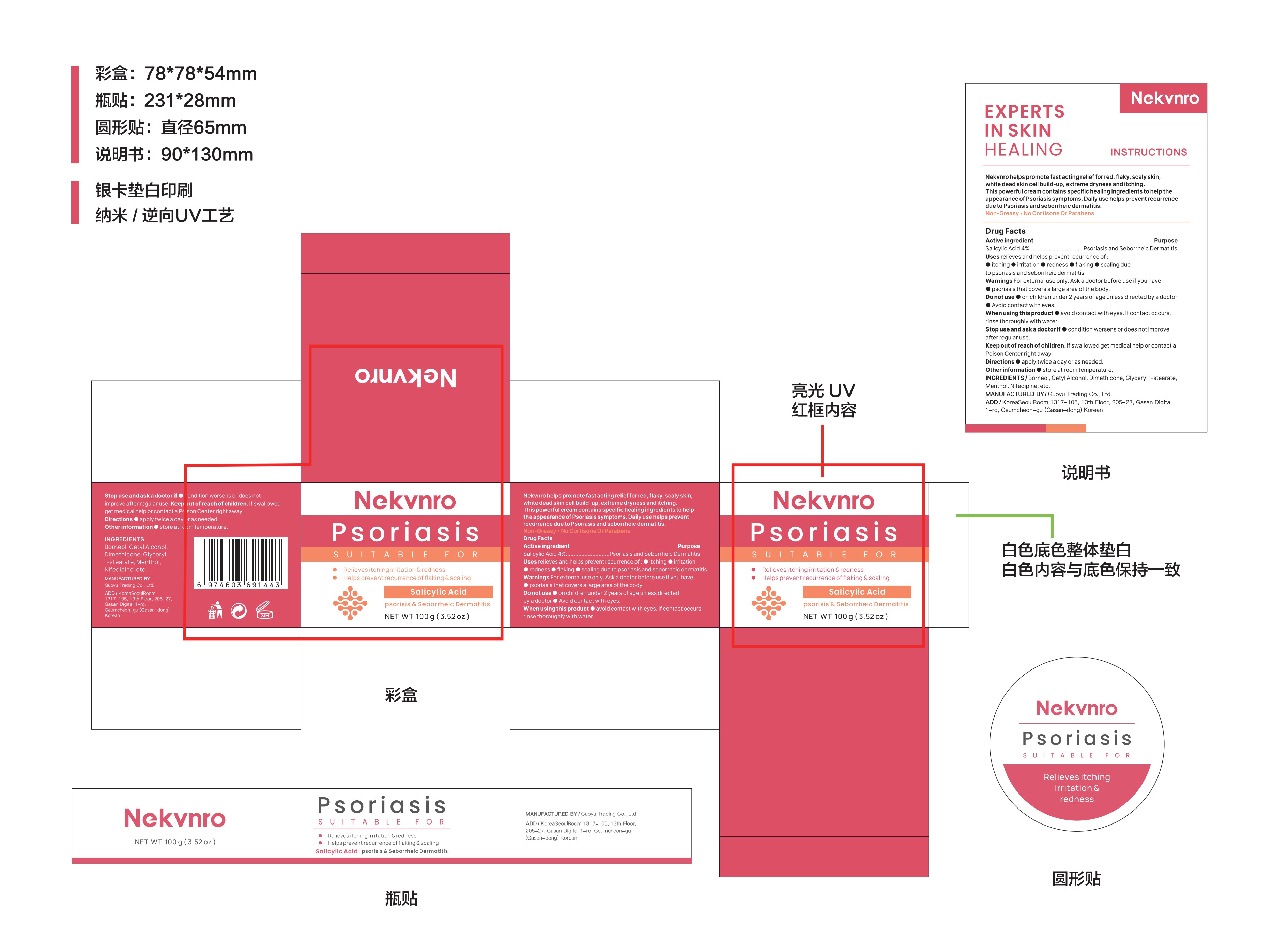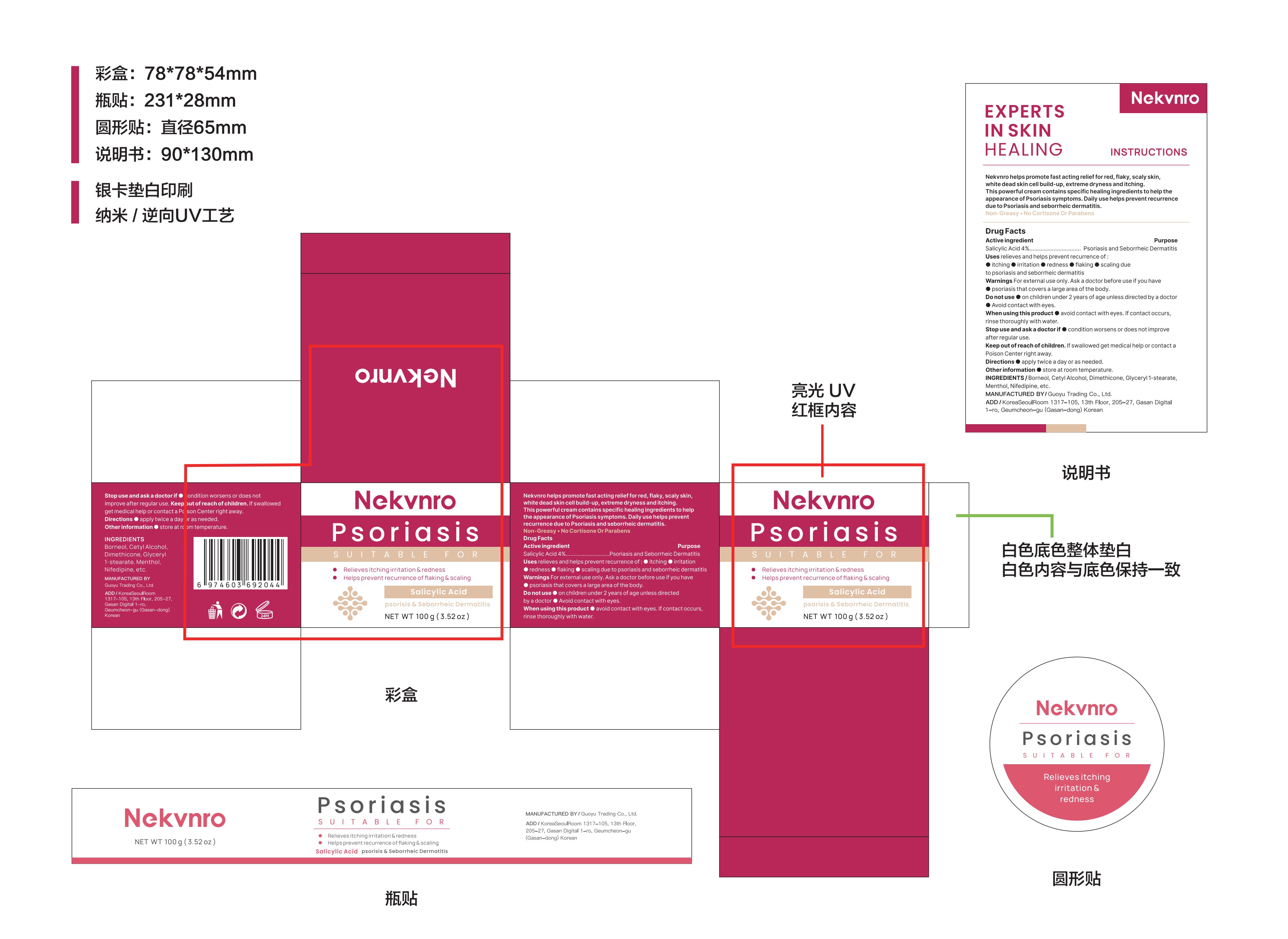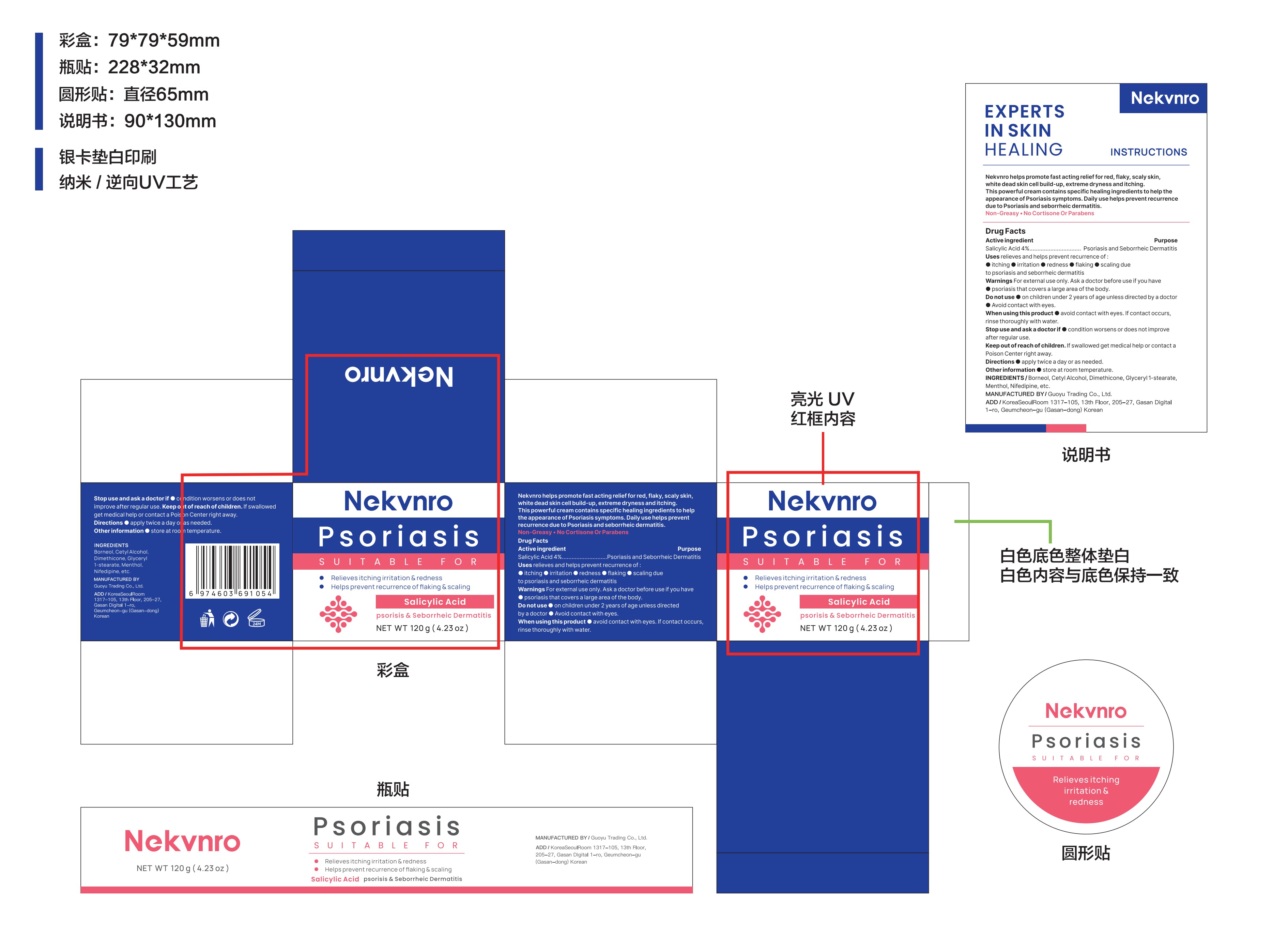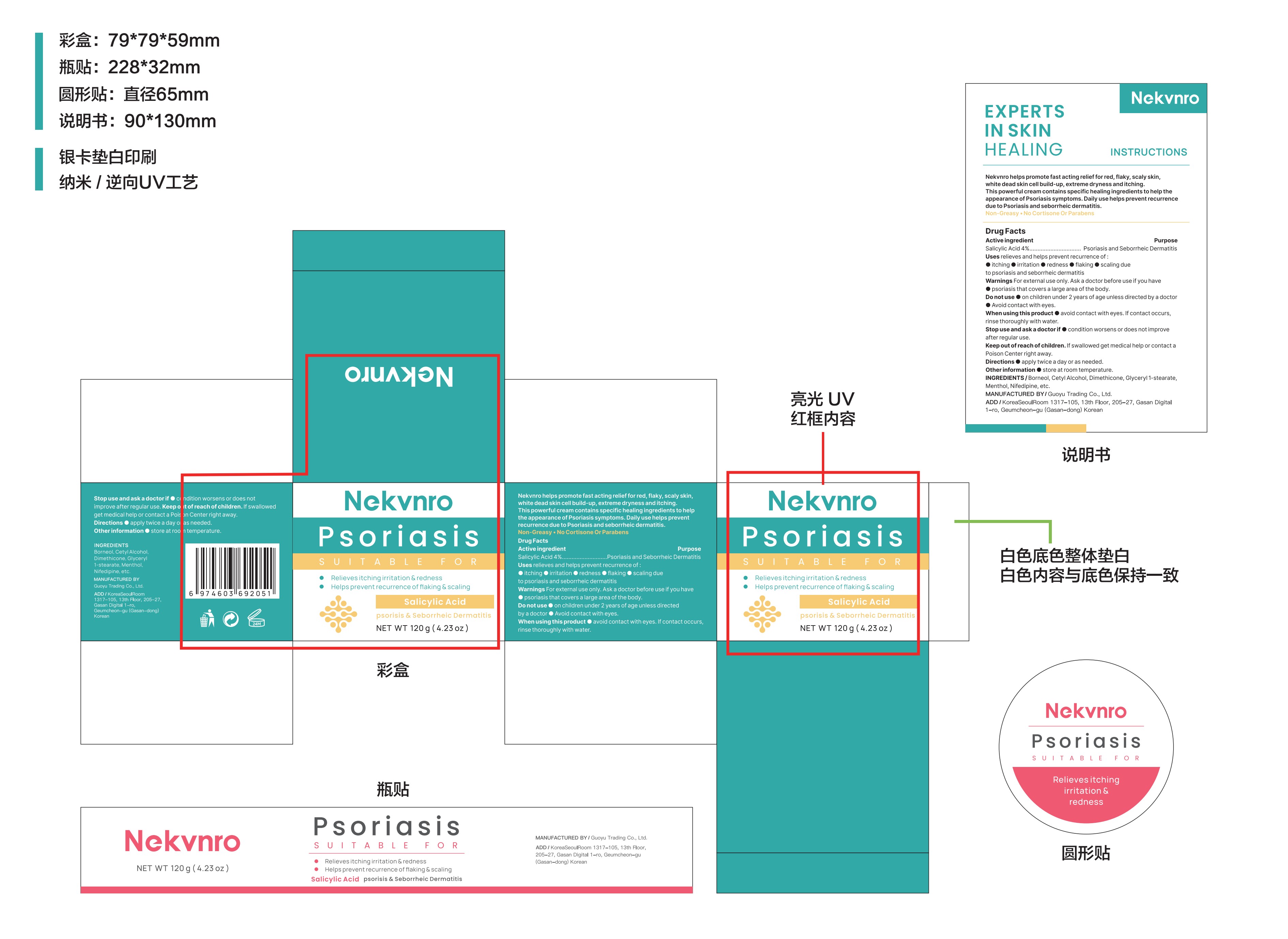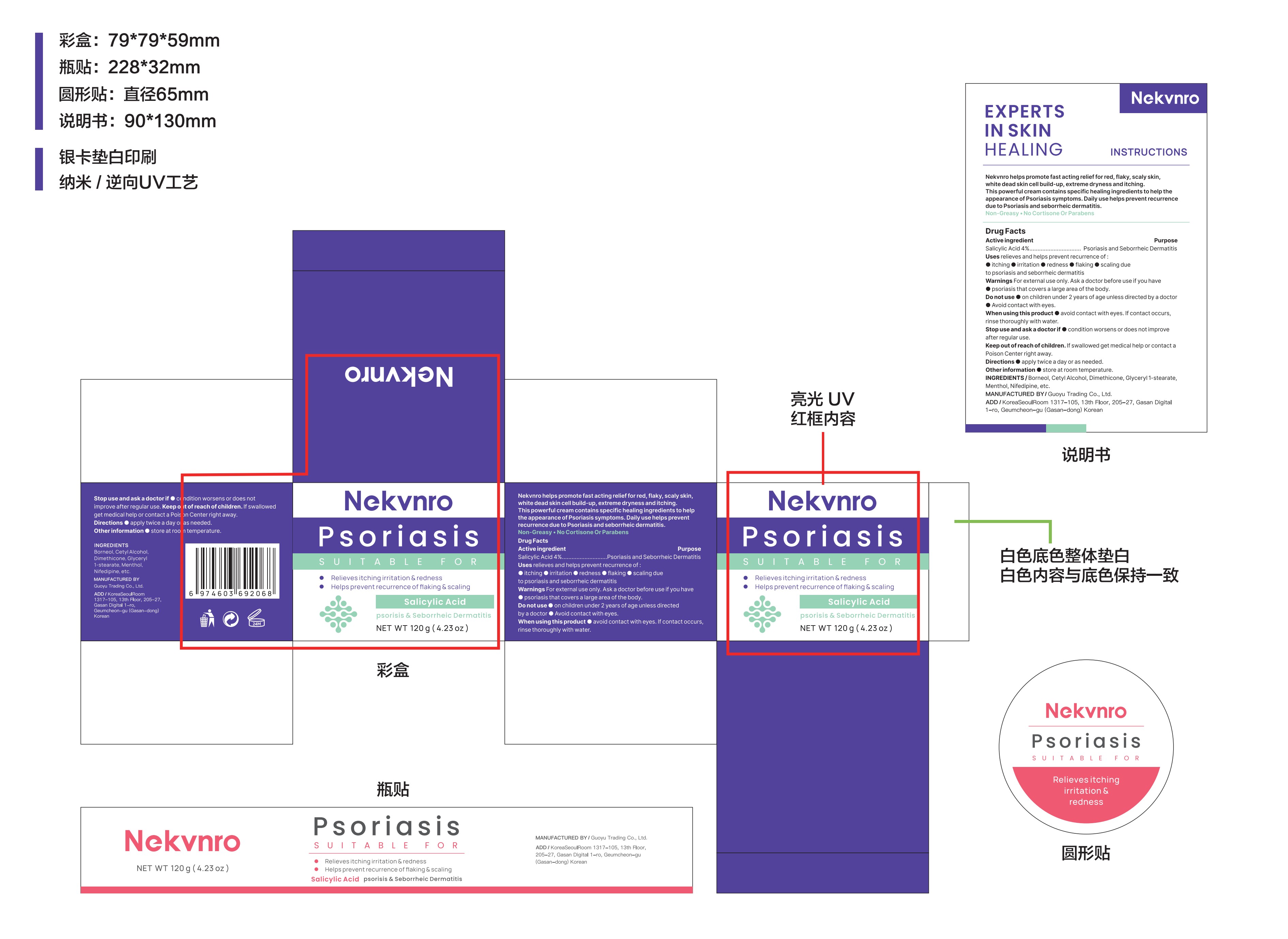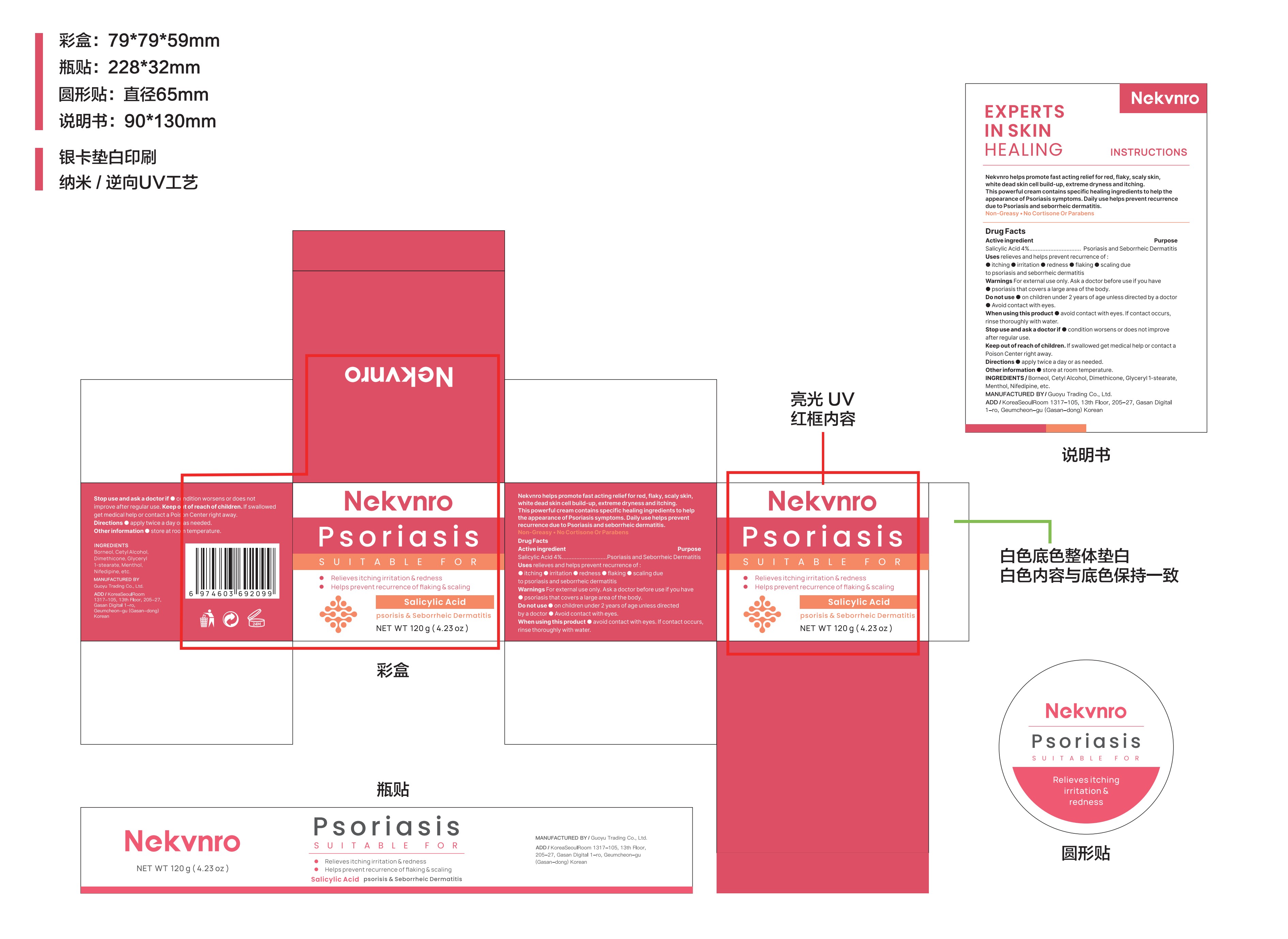 DRUG LABEL: Nekvnro Psoriasis
NDC: 84844-001 | Form: CREAM
Manufacturer: Guoyu Trading Co., Ltd.
Category: otc | Type: HUMAN OTC DRUG LABEL
Date: 20241023

ACTIVE INGREDIENTS: SALICYLIC ACID 4 g/100 g
INACTIVE INGREDIENTS: DIMETHICONE; MENTHOL; BORNEOL; GLYCERYL 1-STEARATE; NIFEDIPINE; CETYL ALCOHOL

84844-001

Active Ingredient

Salicylic Acid 4%

Purpose

Psoriasis and Seborrheic Dermatitis

Use

relieves and helps prevent recurrence of:
■itching

■irritation

■redness

■flaking

■scaling due to psoriasis and seborrheic dermatitis

Do not use

●on children under 2 years of age unless directedby a doctor

●Avoid contact with eyes.

When Using

this product

■avoid contact with eyes. If contact occurs, rinse thoroughly with water.

Stop Use

condition worsens or does not improve after regular use.

Ask Doctor

if condition worsens or does not improve after regular use.

Keep Oot Of Reach Of Children

If swallowed get medical help or contact a Poison Center right away.

Directions

apply twice a day or as needed.

Other information

store at room temperature.

Inactive ingredients

Borneol, Cetyl Alcohol, Dimethicone, Glyceryl 1-stearate, Menthol,Nifedipine, etc.